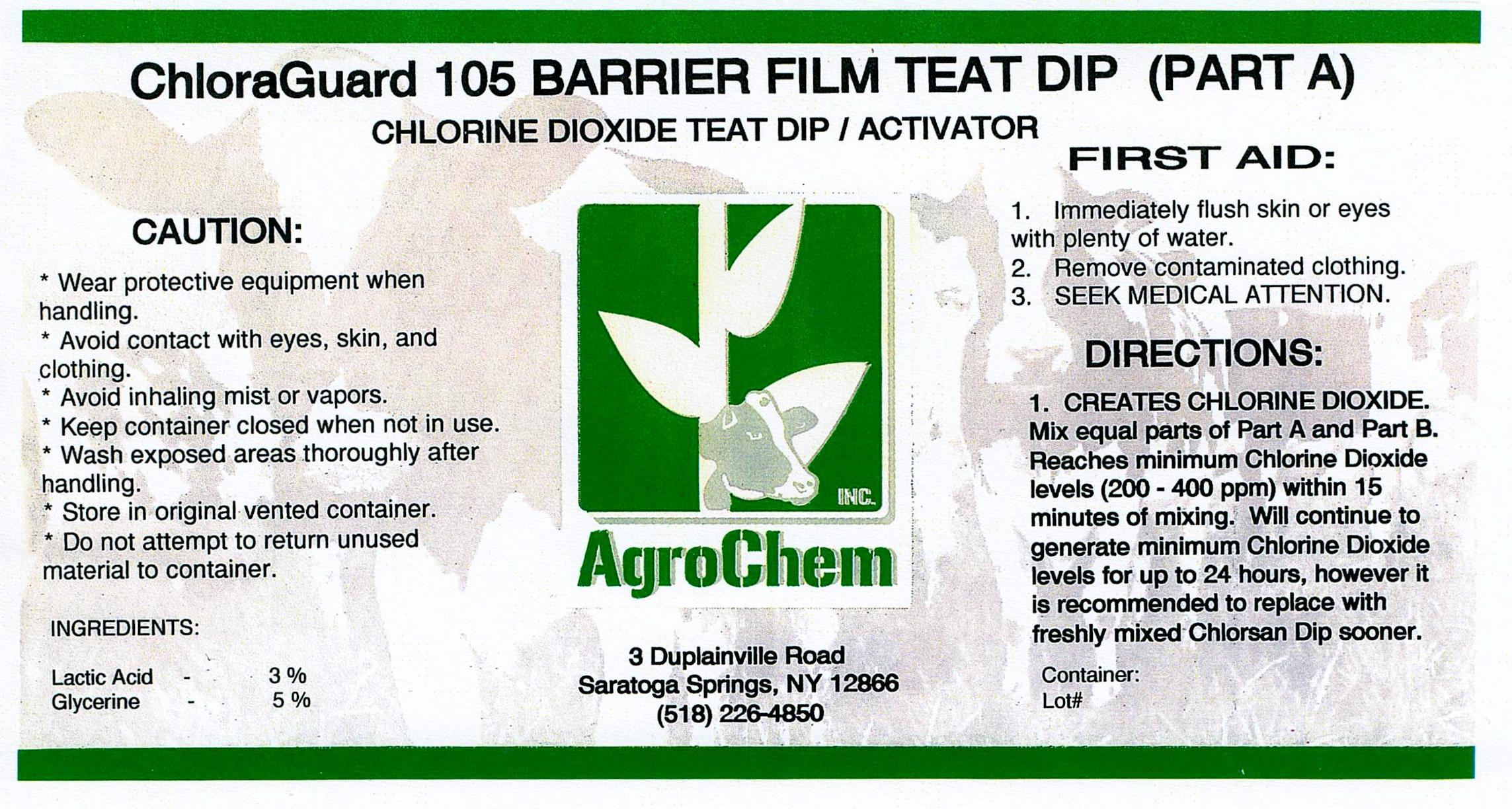 DRUG LABEL: ChloraGuard 105 Part A
NDC: 17307-3610 | Form: SOLUTION
Manufacturer: AgroChem Inc
Category: animal | Type: OTC ANIMAL DRUG LABEL
Date: 20131029

ACTIVE INGREDIENTS: LACTIC ACID 0.03 kg/1 kg
INACTIVE INGREDIENTS: POLYVINYL ALCOHOL 0.05 kg/1 kg; GLYCERIN 0.05 kg/1 kg; DODECYLBENZENESULFONIC ACID 0.01 kg/1 kg; FD&C BLUE NO. 1 0.002 kg/1 kg

ChloraGuard 105 Part A

DESCRIPTION

CHLORINE DIOXIDE TEAT DIP/ACTIVATOR

WARNINGS AND PRECAUTIONS

CAUTION:

* Wear protective equipment when

handling.

* Avoid contact with eyes, skin, and

clothing.

* Avoid inhaling mist or vapors.

* Keep container closed when not in use.

* Wash exposed areas thoroughly after

handling.

* Store in original vented container.

* Do not attempt to return unused material

to container.

ACTIVE INGREDIENT

INGREDIENTS:

Lactic Acid - 3%

Glycerine - 5%

WARNINGS AND PRECAUTIONS

FIRST AID:

1. Immediately flush skin or eyes with

plenty of water.

2. Remove contaminated clothing.

3. SEEK MEDICAL ATTENTION.

DIRECTIONS:

1. CREATES CHLORINE DIOXIDE.

Mix equal parts of Part A and Part

B. Reaches minimum Chlorine

Dioxide levels (200 - 400 ppm)

within 15 minutes of mixing. Will

continue to generate minimum

Chlorine Dioxide levels for up to 24

hours, however it is recommended to

replace with freshly mixed

Chlorsan Dip sooner.